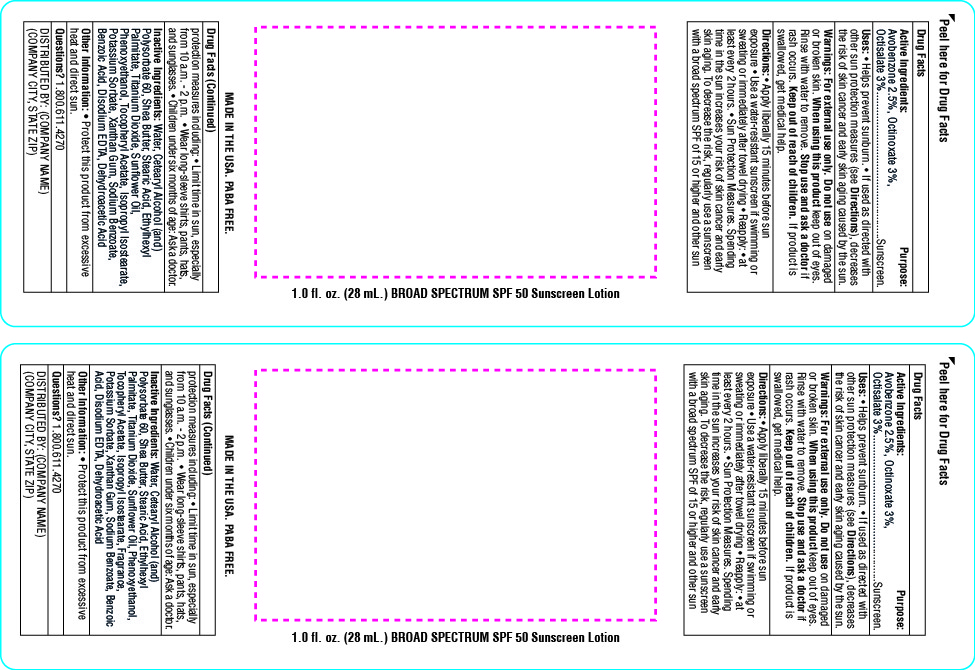 DRUG LABEL: SnugZ SPF 50 Broad Spectrum Sunscreen
NDC: 76309-550 | Form: LOTION
Manufacturer: SnugZ/USA, LLC
Category: otc | Type: HUMAN OTC DRUG LABEL
Date: 20191112

ACTIVE INGREDIENTS: AVOBENZONE 0.85 g/28 mL; OCTINOXATE 2.13 g/28 mL; OCTOCRYLENE 1.42 g/28 mL; OCTISALATE 1.42 g/28 mL
INACTIVE INGREDIENTS: COCONUT OIL

SPF 50 Broad Spectrum Sunscreen Lotion